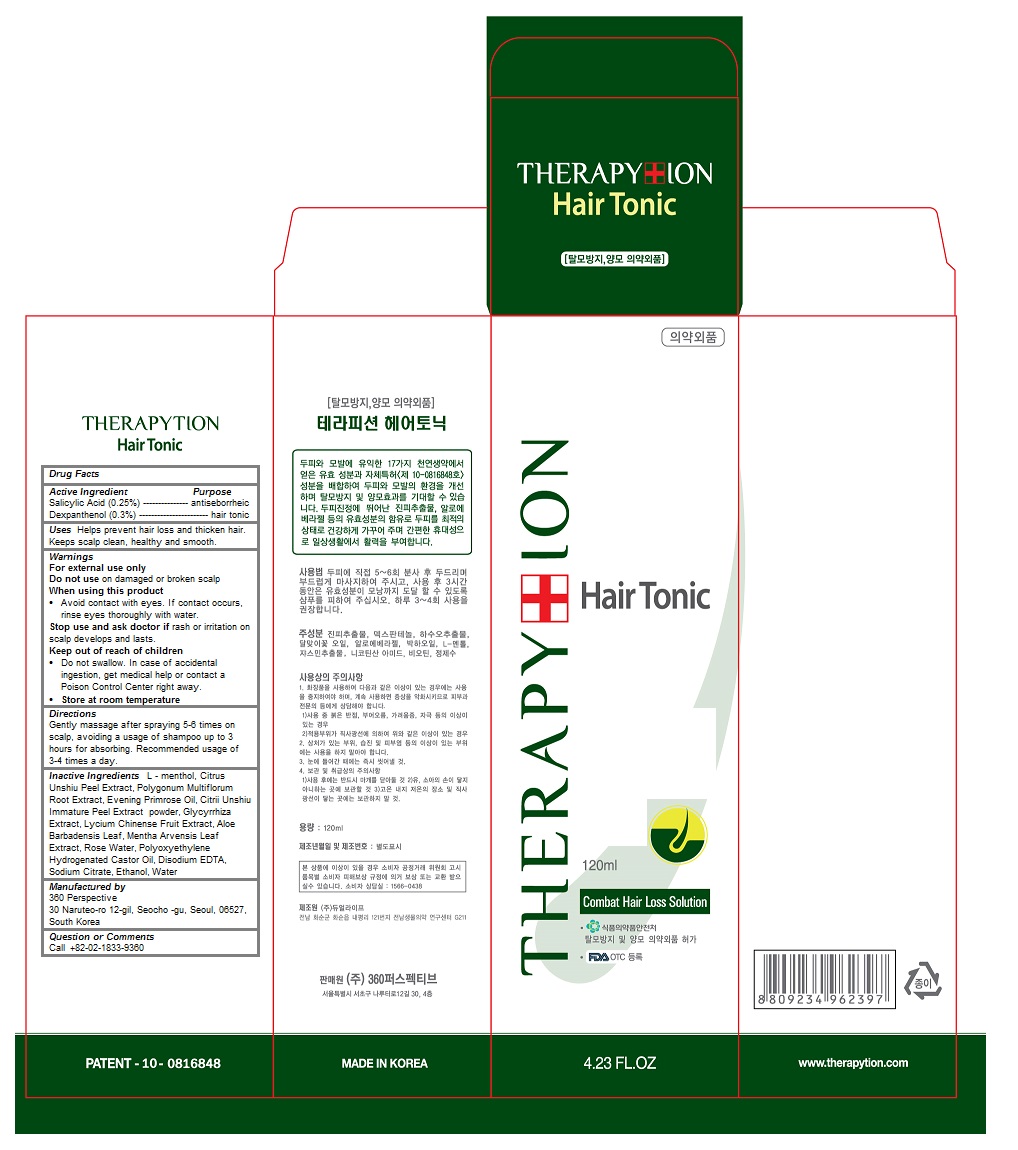 DRUG LABEL: Therapytion Hair Tonic
NDC: 70477-101 | Form: LIQUID
Manufacturer: 360 Perspective
Category: otc | Type: HUMAN OTC DRUG LABEL
Date: 20160229

ACTIVE INGREDIENTS: Salicylic Acid 0.0025 1/120 mL; Dexpanthenol 0.002 1/120 mL
INACTIVE INGREDIENTS: LEVOMENTHOL; TANGERINE PEEL; FALLOPIA MULTIFLORA ROOT; EVENING PRIMROSE OIL; LICORICE; LYCIUM CHINENSE FRUIT; ALOE VERA LEAF; MENTHA ARVENSIS LEAF; PEG-25 HYDROGENATED CASTOR OIL; EDETATE DISODIUM; SODIUM CITRATE, UNSPECIFIED FORM; ALCOHOL; water

Therapytion Hair Tonic